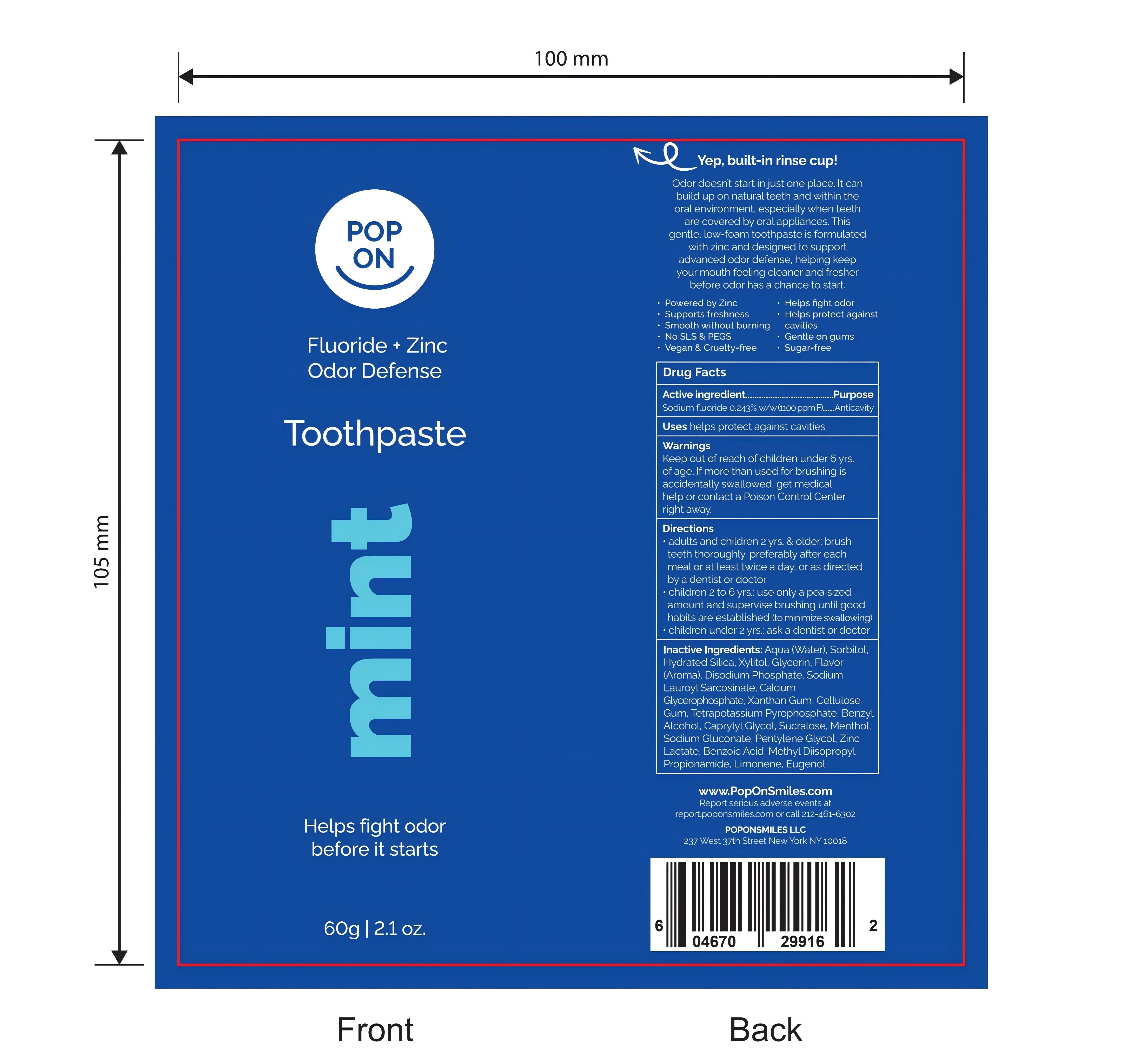 DRUG LABEL: Pop On Toothpaste.
NDC: 87409-001 | Form: PASTE
Manufacturer: POPONSMILES, LLC
Category: otc | Type: HUMAN OTC DRUG LABEL
Date: 20260202

ACTIVE INGREDIENTS: SODIUM FLUORIDE 0.243 g/100 g
INACTIVE INGREDIENTS: FLAVOR SPICE MINT N&A110589; BENZOIC ACID; PENTYLENE GLYCOL; ZINC LACTATE; METHYL DIISOPROPYL PROPIONAMIDE; CAPRYLYL GLYCOL; SORBITOL; DISODIUM PHOSPHATE; SODIUM LAUROYL SARCOSINATE; CALCIUM GLYCEROPHOSPHATE; CARBOXYMETHYLCELLULOSE SODIUM, UNSPECIFIED FORM; GLYCERIN; WATER; HYDRATED SILICA; XANTHAN GUM; SUCRALOSE; TETRAPOTASSIUM PYROPHOSPHATE; XYLITOL; BENZYL ALCOHOL; MENTHOL; SODIUM GLUCONATE

87409-001

Directions

1. Apply 2 pumps to a soft bristle toothbrush.
2. Gently brush it a circular motion for 2 minutes.
3. Expel excess and rinse mouth after use, do not swallow.

Other information

please keep in dry and cool place

Inactive ingredients

Aqua/Water、Sorbitol、Hydrated Silica、Xylitol、Glycerin、Aroma(Flavour)、Disodium Phosphate、Sodium Gluconate、Sodium Lauroyl Sarcosinate、Calcium Glycerophosphate、Cellulose Gum、Xanthan Gum、Tetrapotassium Pyrophosphate、Benzyl Alcohol、Caprylyl Glycol、Sucralose、Menthol、Pentylene Glycol、Zinc Lactate、Methyl Diisopropyl Propionamide、Benzoic Acid.

Purpose

Teeth cleaning

Active Ingredient

Sodium Fluoride

Use

Those who want to clean and whiten their teeth.

Warnings

Product is not intended for use by children. Do not swallow. Do not use in eye area.

Do not use

Product is not intended for use by children.

When Using

Do not swallow. Do not use in eye area.

Stop Use

If there is any discomfort, please stop using.

Ask Doctor

If there is any discomfort, please consult a dentist immediately

Keep Oot Of Reach Of Children

keep out of reach of young children